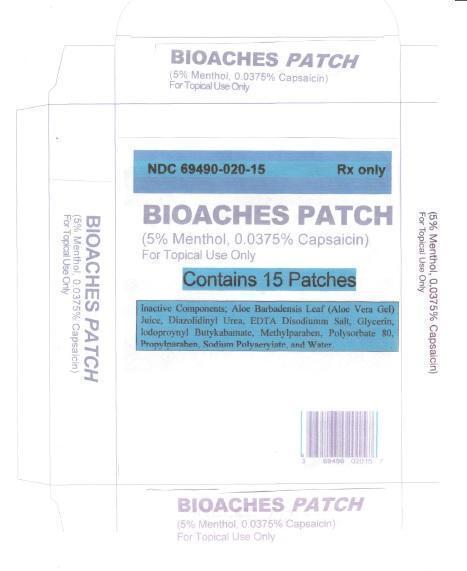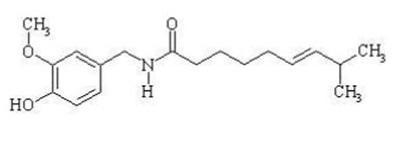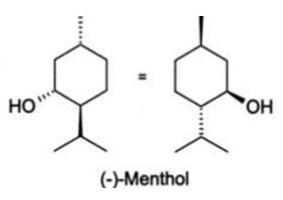 DRUG LABEL: BIOACHES
NDC: 69490-020 | Form: PATCH
Manufacturer: BIO-SANTEE CHEM
Category: prescription | Type: HUMAN PRESCRIPTION DRUG LABEL
Date: 20150109

ACTIVE INGREDIENTS: CAPSAICIN 0.0375 g/1 1; MENTHOL 5 g/1 1
INACTIVE INGREDIENTS: ALOE VERA LEAF; DIAZOLIDINYL UREA; EDETATE DISODIUM; GLYCERIN; IODOPROPYNYL BUTYLCARBAMATE; METHYLPARABEN; POLYSORBATE 80; PROPYLPARABEN; SODIUM POLYACRYLATE (2500000 MW); WATER

BIOACHES

DESCRIPTION:

Bioaches Patch contains capsaicin and menthol in a localized dermal delivery system. The capsaicin in Bioaches Patch is a synthetic equivalent of the naturally occurring compound found in chili peppers. Capsaicin is soluble in alcohol, acetone, and ethyl acetate and very slightly soluble in water. The menthol is slightly soluble in water.
Bioaches Patch is a single-use patch stored in a foil pouch. Each Bioaches Patch is 7.6 cm x 12.7 cm (97 cm²) and consists of a polyester backing film coated with a drug-containing silicone adhesive mixture, and covered with a removable polyester release liner.
The empirical formula for capsaicin is C H NO , with a molecular weight of 305.42. The chemical compound capsaicin [(E)-8-methyl-N-vanillyl-6-nonenamide] is an activating ligand for transient receptor potential vanilloid 1 receptor (TRPV1) and it has the following structure:

The empirical formula for menthol is C H O, with a molecular weight of 156.27. The chemical compound menthol [(1R,2S,5R)-2-isopropyl-5-methylcyclohexanol ] is an activating ligand for transient receptor potential cation channel subfamily M member 8 (TRPM8). It has the following structure:

Each Bioaches Patch contains 0.0375% capsaicin (0.0375 grams of capsaicin per patch) and 5.00% menthol (5 grams of menthol per patch).

INDICATIONS AND USAGE

Bioaches Patch is indicated for the temporary relief of minor aches and muscle pains associated with arthritis, simple backache, strains, muscle soreness and stiffness.
Bioaches Patch is an external analgesic/counterirritant.

CONTRAINDICATIONS

Bioaches Patch is contraindicated for those patients with a history of hypersensitivity to any of the components of the preparation.

WARNINGS

• For external use only.
• Use only as directed.
• Avoid contact with eyes and mucous membranes.
• Do not cover with bandage.
• Do not use on wounds or damaged skin.
• Consult physician for children under 12.
• Do not use if you are allergic to Menthol.
• Stop use and ask a doctor if conditions worsen, symptoms persist for more than 7 days or clear up and occur again within a few days or rash, itching or excessive skin irritation occurs.
• KEEP OUT OF REACH OF CHILDREN

DOSAGE AND ADMINISTRATION

Bioaches patch contains 0.0375% capsaicin and 5.00% menthol

Instructions for Use

Clean and dry affected area
Tear open pouch. Unseal bag and remove patch
Remove protective film and apply directly to area of pain
Apply to affected area not more than 3 times daily
Wash hands with soap after applying patch
Reseal pouch containing unused patches

Directions

Adults and children 12 years and over | - apply to affected area
 | - change patch 1 to 2 times daily
Children under 12 years | - consult physician before use

INACTIVE INGREDIENT

Inactive Components: Aloe Barbadensis Leaf (Aloe Vera Gel) Juice, Diazolidinyl Urea, EDTA Disodium Salt, Glycerin, lodopropynyl Butyl carbamate, Methylparaben, Polysorbate 80, Propylparaben. Sodium Polyacrylate and Water.

HOW SUPPLIED

Bioaches patch is supplied as

Box of 15 patchs: 3 pouches each containing 5 patches

Box of 1 patch: 1 Pouch in one Box

Box of 30 patches: 6 pouches each containing 5 patches.

Storage: Store below 25°C. Avoid direct sunlight.

Rx only